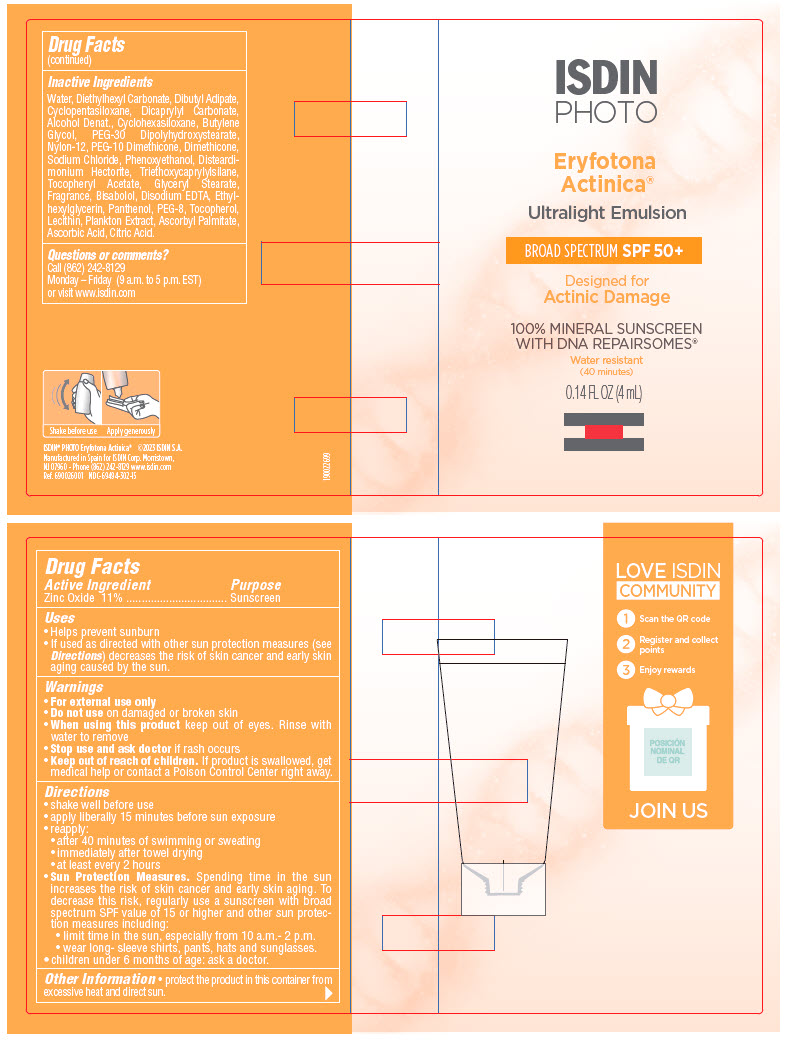 DRUG LABEL: Eryfotona Actinica Ultralight Emulsion
NDC: 69494-302 | Form: EMULSION
Manufacturer: ISDIN Corp
Category: otc | Type: HUMAN OTC DRUG LABEL
Date: 20241118

ACTIVE INGREDIENTS: ZINC OXIDE 11 g/100 mL
INACTIVE INGREDIENTS: SOYBEAN LECITHIN; WATER; DIETHYLHEXYL CARBONATE; Dibutyl Adipate; CYCLOMETHICONE 5; Dicaprylyl Carbonate; Alcohol; DENATONIUM BENZOATE; CYCLOMETHICONE 6; Butylene Glycol; PEG-30 DIPOLYHYDROXYSTEARATE (4000 MW); Nylon-12; PEG-10 DIMETHICONE (600 CST); Dimethicone; Sodium Chloride; Phenoxyethanol; Disteardimonium Hectorite; Triethoxycaprylylsilane; .ALPHA.-TOCOPHEROL ACETATE; GLYCERYL MONOSTEARATE; LEVOMENOL; EDETATE DISODIUM ANHYDROUS; Ethylhexylglycerin; Panthenol; POLYETHYLENE GLYCOL 400; Tocopherol; Ascorbyl Palmitate; Ascorbic Acid; CITRIC ACID MONOHYDRATE; ANACYSTIS NIDULANS

Eryfotona Actinica® Ultralight Emulsion

Drug Facts

Active ingredient

Zinc Oxide 11%

Purpose

Sunscreen

Uses

- Helps prevent sunburn.
- If used as directed with other sun protection measures (see Directions) decreases the risk of skin cancer and early skin aging caused by the sun

Warning

- For external use only.

- Do not use on damaged or broken skin

- When using this product keep out of eyes. Rinse with water to remove.

- Stop use and ask doctor if rash occurs

- Keep out of reach of children. If product is swallowed, get medical help or contact a Poison Control Center right away.

Directions

- Apply liberally 15 minutes before sun exposure
- During sun exposure, reapply:
  - after 40 minutes of swimming or sweating
  - immediately after towel drying
  - at least every 2 hours
- Sun Protection Measures: Spending time in the sun increases the risk of skin cancer and early skin aging. To decrease this risk, regularly use a sunscreen with broad spectrum SPF value of 15 or higher and other sun protection measures including:
  - limit time in the sun, especially from 10 a.m.- 2 p.m.
  - wear long- sleeve shirts, pants, hats and sunglasses
- Children under 6 months: ask a doctor.

Other information

- Protect the product in this container from excessive heat and direct sun.

Inactive ingredients

Water, Diethylhexyl Carbonate, Dibutyl Adipate, Cyclopentasiloxane, Dicaprylyl Carbonate, Alcohol Denat., Cyclohexasiloxane, Butylene Glycol, PEG-30 Dipolyhydroxystearate, Nylon-12, PEG-10 Dimethicone, Dimethicone, Sodium Chloride, Phenoxyethanol, Disteardimonium Hectorite, Triethoxycaprylylsilane, Tocopheryl Acetate, Glyceryl Stearate, Fragrance, Bisabolol, Disodium EDTA, Ethylhexylglycerin, Panthenol, PEG-8, Tocopherol, Lecithin, Plankton Extract, Ascorbyl Palmitate, Ascorbic Acid, Citric Acid.

Questions or comments?

Call (862) 242-8129
Monday – Friday
(9 a.m. to 5 p.m. EST)
or visit www.isdin/us
USA Patent Pending

PRINCIPAL DISPLAY PANEL - 4 mL Tube Packet

ISDIN
PHOTO

Eryfotona
Actinica®

Ultralight Emulsion

BROAD SPECTRUM SPF 50+

Designed for
Actinic Damage

100% MINERAL SUNSCREEN
WITH DNA REPAIRSOMES®

Water resistant
(40 minutes)

0.14 FL OZ (4 mL)